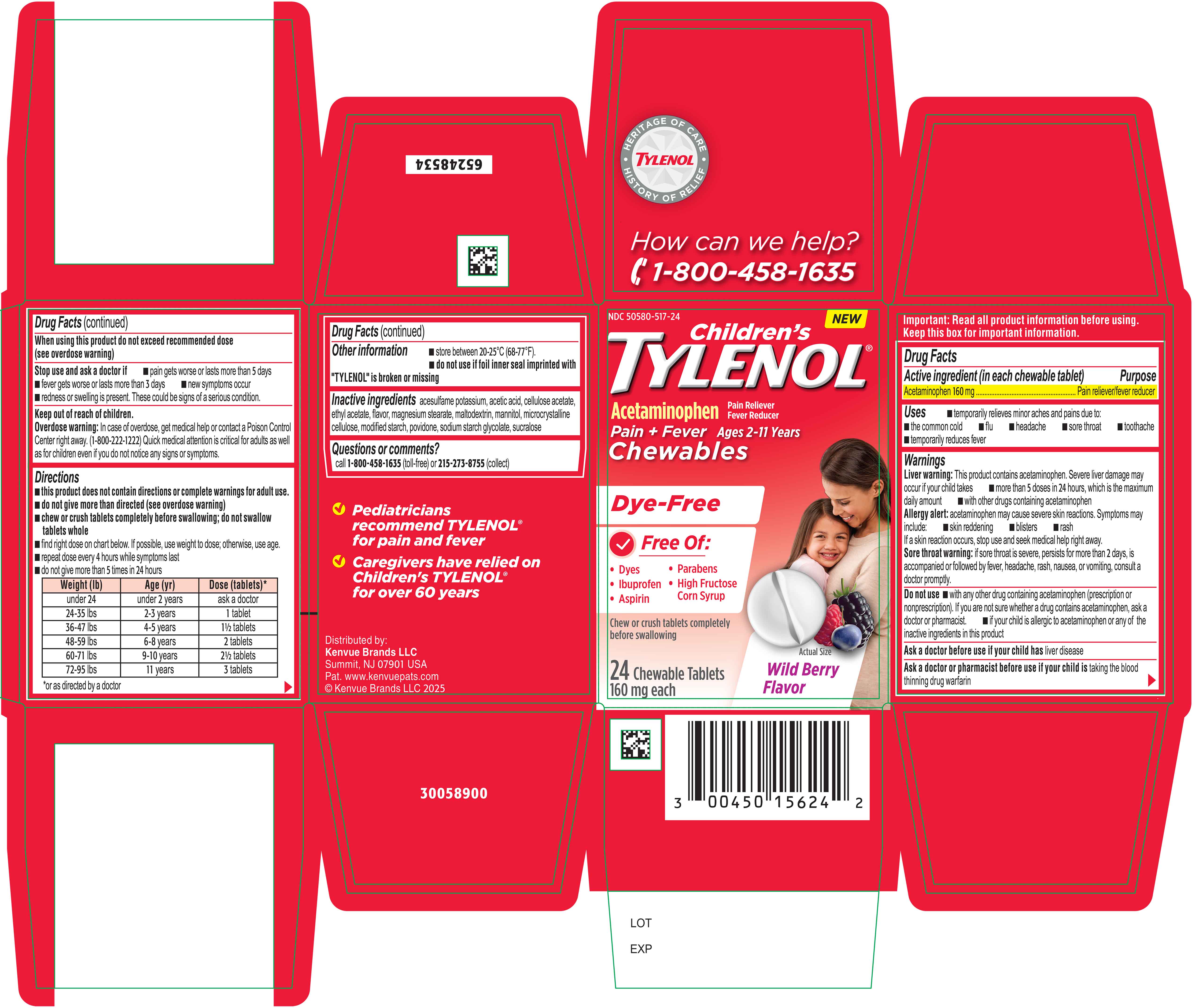 DRUG LABEL: Childrens TYLENOL
NDC: 50580-517 | Form: TABLET, CHEWABLE
Manufacturer: Kenvue Brands LLC
Category: otc | Type: HUMAN OTC DRUG LABEL
Date: 20250723

ACTIVE INGREDIENTS: ACETAMINOPHEN 160 mg/1 1
INACTIVE INGREDIENTS: ACESULFAME POTASSIUM; ACETIC ACID; CELLULOSE ACETATE; ETHYL ACETATE; MALTODEXTRIN; MAGNESIUM STEARATE; MANNITOL; MICROCRYSTALLINE CELLULOSE; POVIDONE, UNSPECIFIED; SODIUM STARCH GLYCOLATE TYPE A; SUCRALOSE

Children’s TYLENOL

Drug Facts

Active ingredient (in each chewable tablet)

Acetaminophen 160 mg

Purpose

Pain reliever/fever reducer

Uses

- temporarily relieves minor aches and pains due to:
- the common cold
- flu
- headache
- sore throat
- toothache

- temporarily reduces fever

Warnings

Liver warning

This product contains acetaminophen. Severe liver damage may occur if your child takes

- more than 5 doses in 24 hours, which is the maximum daily amount
- with other drugs containing acetaminophen

Allergy alert

acetaminophen may cause severe skin reactions. Symptoms may include:

- skin reddening
- blisters
- rash

If a skin reaction occurs, stop use and seek medical help right away.

Sore throat warning

if sore throat is severe, persists for more than 2 days, is accompanied or followed by fever, headache, rash, nausea, or vomiting, consult a doctor promptly.

Do not use

- with any other drug containing acetaminophen (prescription or nonprescription). If you are not sure whether a drug contains acetaminophen, ask a doctor or pharmacist.
- if your child is allergic to acetaminophen or any of the inactive ingredients in this product

Ask a doctor before use if your child has liver disease

Ask a doctor or pharmacist before use if your child is taking the blood thinning drug warfarin

When using this product do not exceed recommended dose
(see overdose warning)

Stop use and ask a doctor if

- pain gets worse or lasts more than 5 days
- fever gets worse or lasts more than 3 days
- new symptoms occur
- redness or swelling is present.

These could be signs of a serious condition.

Keep out of reach of children.

Overdose warning

In case of overdose, get medical help or contact a Poison Control Center right away. (1-800-222-1222) Quick medical attention is critical for adults as well as for children even if you do not notice any signs or symptoms.

Directions

- this product does not contain directions or complete warnings for adult use.
- do not give more than directed (see overdose warning)
- chew or crush tablets completely before swallowing; do not swallow tablets whole
- find right dose on chart below. If possible, use weight to dose; otherwise, use age.
- repeat dose every 4 hours while symptoms last
- do not give more than 5 times in 24 hours

Weight (lb) | Age (yr) | Dose (tablets)*
under 24 | under 2 years | ask a doctor
24-35 lbs | 2-3 years | 1 tablet
36-47 lbs | 4-5 years | 1½ tablets
48-59 lbs | 6-8 years | 2 tablets
60-71 lbs | 9-10 years | 2½ tablets
72-95 lbs | 11 years | 3 tablets

*or as directed by a doctor

Other information

- store between 20-25°C (68-77°F).
- do not use if foil inner seal imprinted with "TYLENOL" is broken or missing

Inactive ingredients

acesulfame potassium, acetic acid, cellulose acetate, ethyl acetate, flavor, magnesium stearate, maltodextrin, mannitol, microcrystalline cellulose, modified starch, povidone, sodium starch glycolate, sucralose

Questions or comments?

call 1-800-458-1635 (toll-free) or 215-273-8755 (collect)

PRINCIPAL DISPLAY PANEL

NDC 50580-517-24

NEW

Children’s

TYLENOL®

Acetaminophen
Pain + Fever Ages 2-11 Years

Chewables

Pain Reliever

Fever Reducer

Dye-Free

Free Of:

• Dyes
• Ibuprofen
• Aspirin
• Parabens
• High Fructose Corn Syrup

Chew or crush tablets completely

before swallowing

24 Chewable Tablets
160 mg each

Actual Size
Wild Berry
Flavor